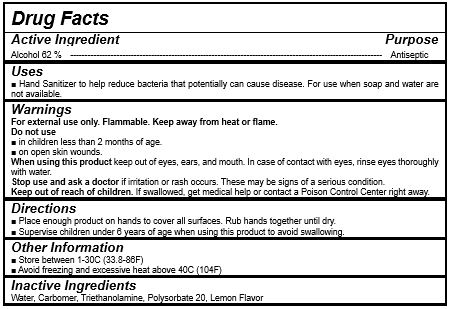 DRUG LABEL: DOCTOR HAND FRESH Gel
NDC: 70949-002 | Form: GEL
Manufacturer: C-MAX KOREA CO.,LTD.
Category: otc | Type: HUMAN OTC DRUG LABEL
Date: 20200403

ACTIVE INGREDIENTS: ALCOHOL 310 mL/500 mL
INACTIVE INGREDIENTS: PEPPERMINT; TROLAMINE; WATER; POLYSORBATE 60

Drug Facts

ACTIVE INGREDIENT

ethanol

INACTIVE INGREDIENT

water, carbopol, polysorbate 60, triethanolamine, peppermint oil

PURPOSE

Antiseptic

instant healthcare personnel hand antiseptic to reduce bacteria that potentially can cause disease

instant hand antiseptic to decrease bacteria on the skin
recommended for repeated use

KEEP OUT OF REACH OF THE CHILDREN

INDICATIONS AND USAGE

Apply to clean, dry hands. Apply sufficient amount to thoroughly wet all surfaces of hands and fingers. Rub onto hands until dry.

Supervise children in the use of this product.

WARNINGS

For external use only.

Flammable, keep away from fire or flame.

When using this product keep out of eyes. If contact with eyes occurs, rinse promptly and thoroughly with water.

Stop use and ask a doctor if significant irritation or sensitization develops.

Keep out of reach of children. If swallowed, get medical help or contact a Poison Control Center right away.

DOSAGE AND ADMINISTRATION

for external use only